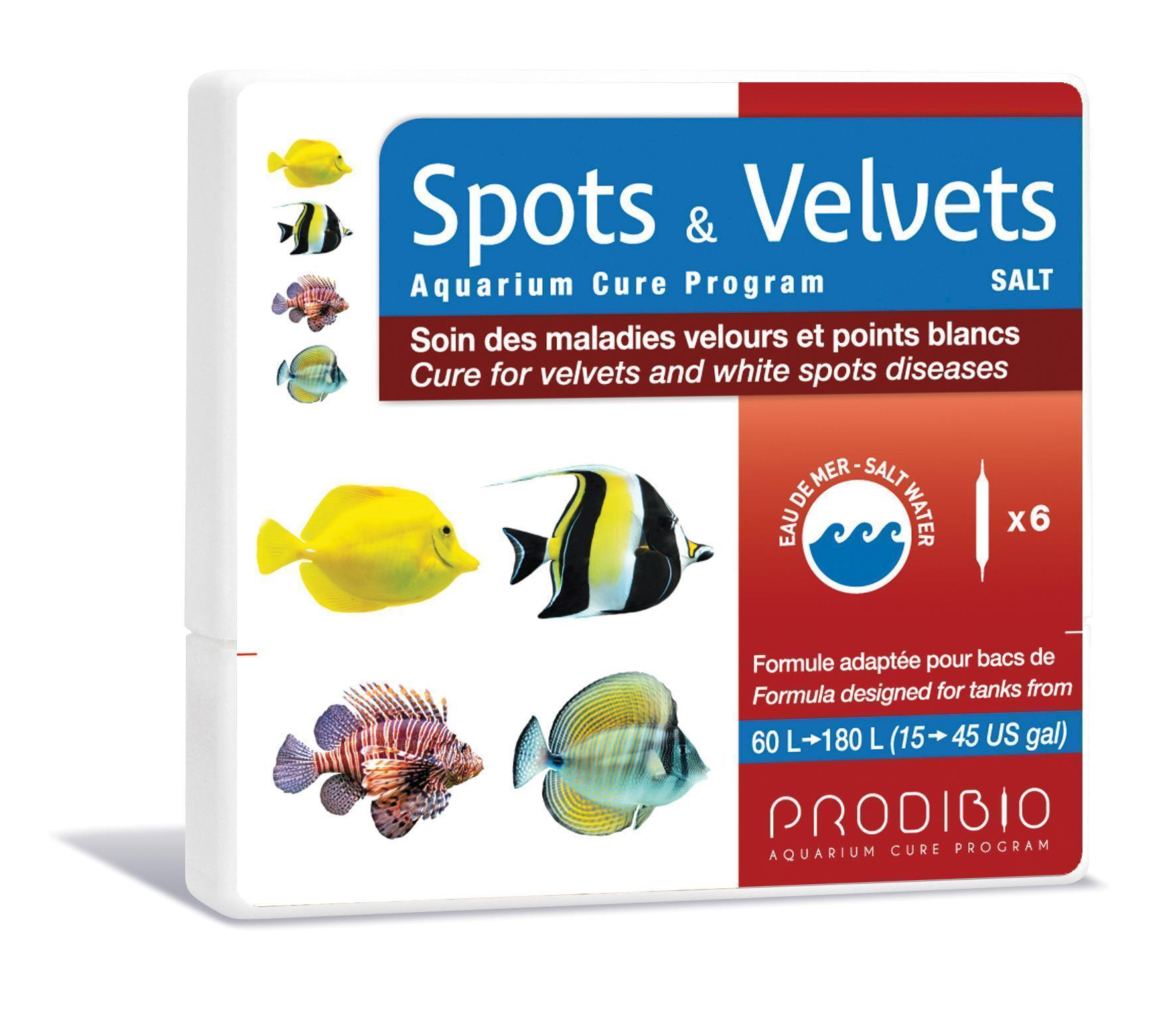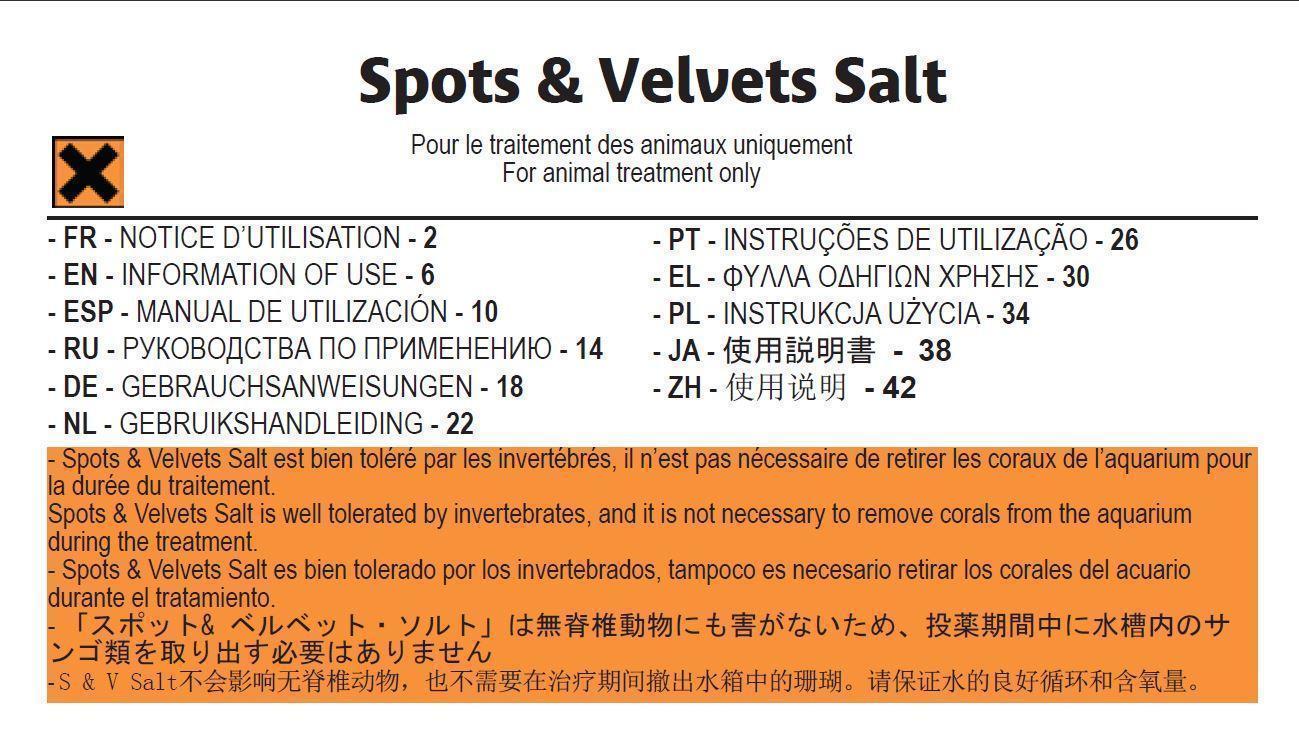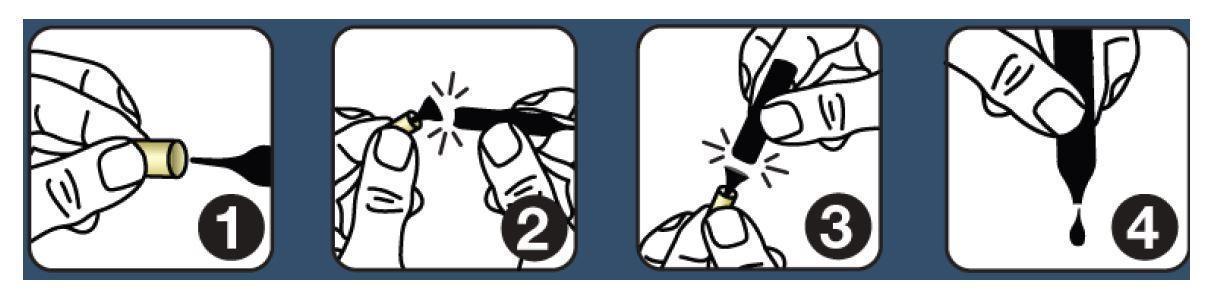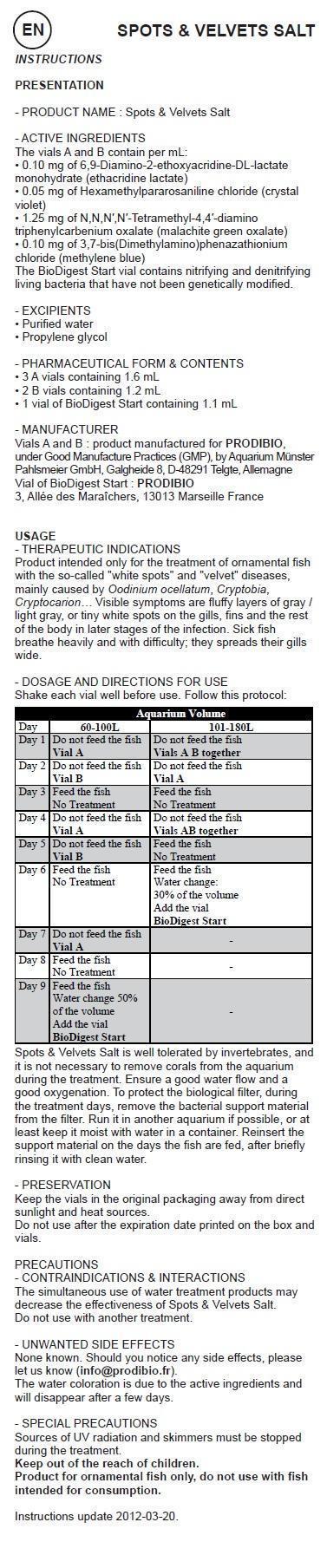 DRUG LABEL: SPOTS and VELVETS Aquarium Cure Program SALT
NDC: 86048-006 | Form: KIT | Route: ORAL
Manufacturer: Prodibio SAS
Category: animal | Type: OTC ANIMAL DRUG LABEL
Date: 20150902

ACTIVE INGREDIENTS: GENTIAN VIOLET 0.05 mg/1 mL; MALACHITE GREEN OXALATE 1.25 mg/1 mL; ETHACRIDINE LACTATE 0.10 mg/1 mL; METHYLENE BLUE 0.10 mg/1 mL; ETHACRIDINE LACTATE 0.10 mg/1 mL; GENTIAN VIOLET 0.05 mg/1 mL; MALACHITE GREEN OXALATE 1.25 mg/1 mL; METHYLENE BLUE 0.10 mg/1 mL
INACTIVE INGREDIENTS: WATER; PROPYLENE GLYCOL; WATER; PROPYLENE GLYCOL

SPOTS & VELVETS Aquarium Cure Program SALT

-PRODUCT NAME : Spots & Velvets Salt

- ACTIVE INGREDIENTS

The vials A and B contain per mL:
• 0.10 mg of 6,9-Diamino-2-ethoxyacridine-DL-lactate monohydrate (ethacridine lactate)
• 0.05 mg of Hexamethylpararosaniline chloride (crystal violet)
• 1.25 mg of N,N,N′,N′-Tetramethyl-4,4′-diamino triphenylcarbenium oxalate (malachite green oxalate)
• 0.10 mg of 3,7-bis(Dimethylamino)phenazathionium chloride (methylene blue)
The BioDigest Start vial contains nitrifying and denitrifying living bacteria that have not been genetically modified.

- EXCIPIENTS

• Purified water
• Propylene glycol

- PHARMACEUTICAL FORM & CONTENTS

• 3 A vials containing 1.6 mL
• 2 B vials containing 1.2 mL
• 1 vial of BioDigest Start containing 1.1 mL

- MANUFACTURER

Vials A and B : product manufactured for PRODIBIO,
under GMP, by Aquarium Münster Pahlsmeier GmbH,
Galgheide 8, D-48291 Telgte, GE
Vial of BioDigest Start : PRODIBIO
3, Allée des Maraîchers, 13013 Marseille, France

USAGE

- THERAPEUTIC INDICATIONS
Product intended only for the treatment of ornamental fish with the so-called "white spots" and "velvet" diseases, mainly caused by Oodinium ocellatum, Cryptobia, Cryptocarion… Visible symptoms are fluffy layers of gray / light gray, or tiny white spots on the gills, fins and the rest of the body in later stages of the infection. Sick fish breathe heavily and with difficulty; they spreads their gills wide.

- DOSAGE AND DIRECTIONS FOR USE

Shake each vial well before use. Follow this protocol:

Days | 60-100L | 101-180L
Day 1 | Do not feed the fish Vial A | Do not feed the fish Vials A B together
Day 2 | Do not feed the fish; Vial B | Do not feed the fish Vials A
Day 3 | Feed the fish No Treatment | Feed the fish No Treatment
Day 4 | Do not feed the fish Vial A | Do not feed the fish Vials AB together
Day 5 | Do not feed the fish; Vial B | Feed the fish No Treatment
Day 6 | Feed the fish No Treatment | Feed the fish Water change: 30% of the volume Add the vial BioDigest Start
Day 7 | Do not feed the fish Vial A | -
Day 8 | Feed the fish No Treatment | -
Day 9 | Feed the fish; Water change 50% of the volume- Add the vial BioDigest Start | -

Spots & Velvets Salt is well tolerated by invertebrates, and it is not necessary to remove corals from the aquarium during the treatment. Ensure a good water flow and a good oxygenation. To protect the biological filter, during the treatment days, remove the bacterial support material from the filter. Run it in another aquarium if possible, or at least keep it moist with water in a container. Reinsert the support material on the days the fish are fed, after briefly rinsing it with clean water.

- PRESERVATION

Keep the vials in the original packaging away from direct sunlight and heat sources.
Do not use after the expiration date printed on the box and vials.

PRECAUTIONS - CONTRAINDICATIONS & INTERACTIONS

The simultaneous use of water treatment products may decrease the effectiveness of Spots & Velvets Salt.
Do not use with another treatment.

- UNWANTED SIDE EFFECTS

None known. Should you notice any side effects, please let us know (info@prodibio.fr).
The water coloration is due to the active ingredients and will disappear after a few days.

- SPECIAL PRECAUTIONS

Sources of UV radiation and skimmers must be stopped during the treatment.
Product for ornamental fish only, do not use with fish intended for consumption.

This veterinary medicines is marketed in accordinance with the Small Animal Exception Scheme

Instructions update 2012-08.

- Special precautions for the disposal of unused pharmaceuticals

Dispose od drugs not entirely used up at the respective collecting points

Disposal advice: after use, vials must be thrown in recyclable glass rubbish